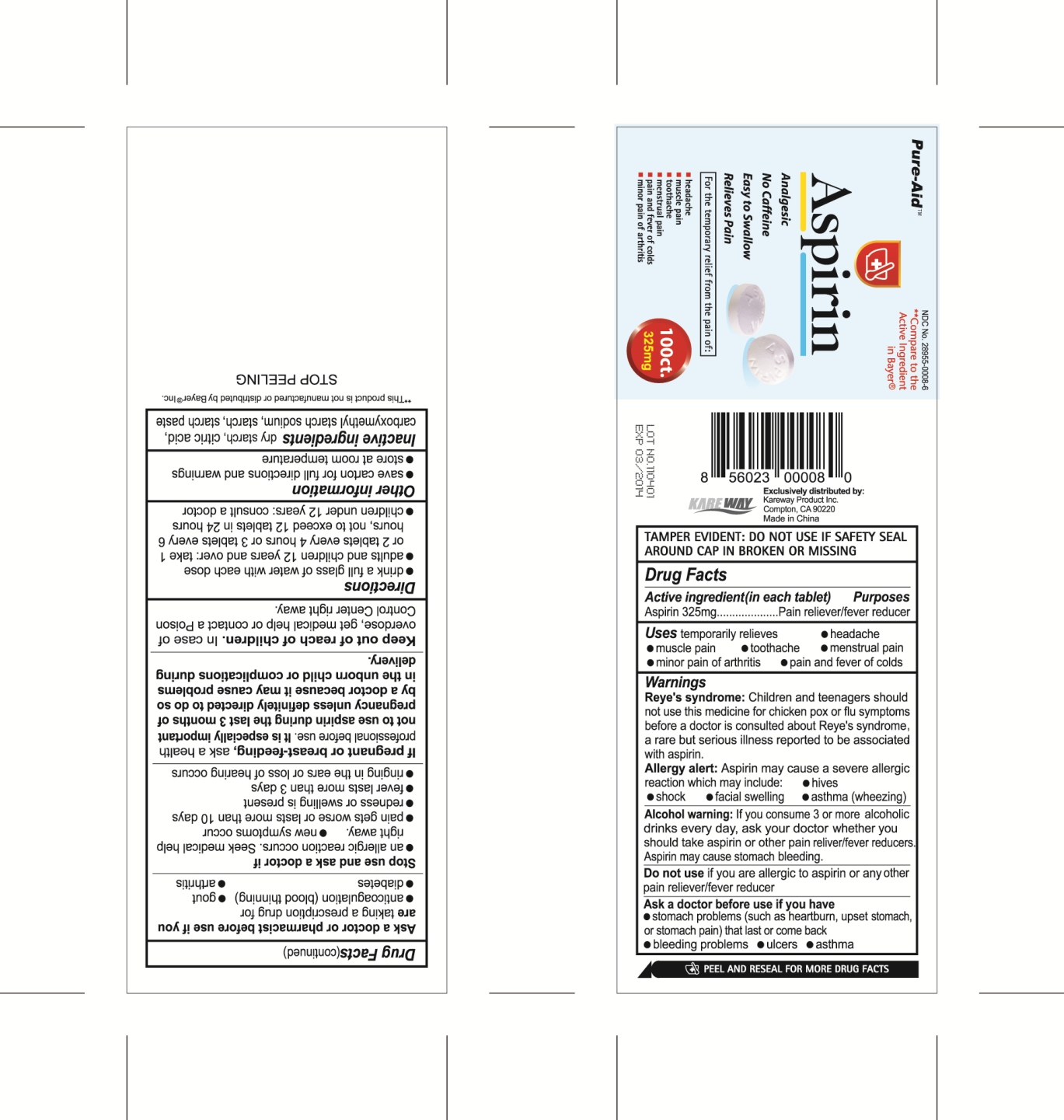 DRUG LABEL: Aspirin
NDC: 67510-0008 | Form: TABLET
Manufacturer: Kareway Product, Inc.
Category: otc | Type: HUMAN OTC DRUG LABEL
Date: 20111123

ACTIVE INGREDIENTS: ASPIRIN 325 mg/1 1
INACTIVE INGREDIENTS: CITRIC ACID MONOHYDRATE; CARBOXYMETHYLCELLULOSE SODIUM; STARCH, CORN

Drug Facts

Active ingredient(in each tablet)

Aspirin 325mg

Purposes

Pain reliever/fever reducer

Uses

temporarily relieves

- headache
- muscle pain
- toothache
- menstrual pain
- minor pain of arthritis
- pain and fever of colds

Warnings

Reye's syndrome:Children and teenagers should not use this medicine for chicken pox or flu symptoms before a doctor is consulted about Reye's syndrome, a rare but serious illness reported to be associated with aspirin.

Allergy alert:Aspirin may cause a severe allergic reaction which may include:

- hives
- shock
- facial swelling
- asthma (wheezing)

Alcohol warning:

If you consume 3 or more alcoholic drinks every day, ask your doctor whether you should take aspirin or other pain reliever/fever reducers. Aspirin may cause stomach bleeding.

Do not use

if you are allergic to aspirin or any other pain reliever/fever reducer

Ask a doctor before use if you have

- stomach problems (such as heartburn, upset stomach, or stomach pain) that last or come back
- bleeding problems
- ulcers
- asthma

Ask a doctor or pharmacist before use if you are

taking a prescription drug for

- anticoagulation (blood thinning)
- gout
- diabetes
- arthritis

Stop use and ask a doctor if

- an allergic reaction occurs. Seek medical help right away.
- new symptoms occur
- pain gets worse or lasts more than 10 days
- redness or swelling is present
- fever lasts more than 3 days
- ringing in the ears or loss of hearing occurs

If pregnant or breast-feeding,

ask a health professional before use.It is especially important not to use aspirin during the last 3 months of pregnancy unless definitely directed to do so by a doctor because it may cause problems in the unborn child or complications during delivery.

Keep out of reach of children.

In case of overdose, get medical help or contact a Poison Control Center right away.

Directions

- drink a full glass of water with each dose
- adults and children 12 years and over: take 1 or 2 tablets every 4 hours or 3 tablets every 6 hours, not to exceed 12 tablets in 24 hours
- children under 12 years: consult a doctor

Other information

- save carton for full directions and warnings
- store at room temperature

Inactive ingredients

dry starch, citric acid, carboxymethyl starch sodium, starch, starch paste

PACKAGE LABEL

Aspirin